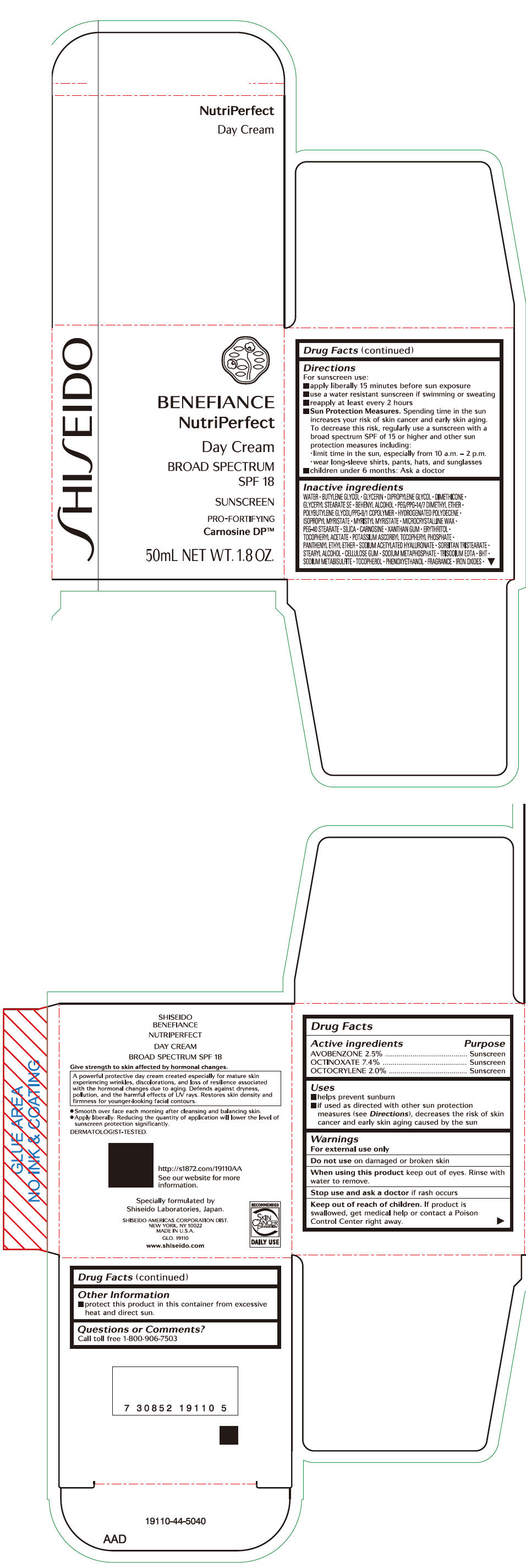 DRUG LABEL: SHISEIDO BENEFIANCE NUTRIPERFECT DAY
NDC: 58411-351 | Form: CREAM
Manufacturer: SHISEIDO AMERICAS CORPORATION
Category: otc | Type: HUMAN OTC DRUG LABEL
Date: 20260204

ACTIVE INGREDIENTS: AVOBENZONE 1286 mg/51.45 g; OCTINOXATE 3807 mg/51.45 g; OCTOCRYLENE 1029 mg/51.45 g
INACTIVE INGREDIENTS: WATER; BUTYLENE GLYCOL; GLYCERIN; DIPROPYLENE GLYCOL; DIMETHICONE; GLYCERYL MONOSTEARATE; DOCOSANOL; PEG/PPG-14/7 DIMETHYL ETHER; HYDROGENATED POLYDECENE TYPE I; ISOPROPYL MYRISTATE; MYRISTYL MYRISTATE; PEG-40 MONOSTEARATE; CARNOSINE; SILICON DIOXIDE; SORBITAN TRISTEARATE; MICROCRYSTALLINE WAX; STEARYL ALCOHOL; PHENOXYETHANOL; XANTHAN GUM; CARBOXYMETHYLCELLULOSE SODIUM, UNSPECIFIED; SODIUM POLYMETAPHOSPHATE; ERYTHRITOL; EDETATE TRISODIUM; .ALPHA.-TOCOPHEROL ACETATE, DL-; PANTHENYL ETHYL ETHER; POTASSIUM ASCORBYL TOCOPHERYL PHOSPHATE; FERRIC OXIDE RED; FERRIC OXIDE YELLOW; BUTYLATED HYDROXYTOLUENE; SODIUM METABISULFITE; .ALPHA.-TOCOPHEROL

SHISEIDO BENEFIANCE NUTRIPERFECT DAY

Drug Facts

ACTIVE INGREDIENT

ACTIVE INGREDIENTS: | Purpose
AVOBENZONE 2.5% | Sunscreen
OCTINOXATE 7.4% | Sunscreen
OCTOCRYLENE 2.0% | Sunscreen

Uses

- helps prevent sunburn
- if used as directed with other sun protection measures (see Directions), decreases the risk of skin cancer and early skin aging caused by the sun

Warnings

For external use only

Do not useon damaged or broken skin

WHEN USING

When using this productkeep out of eyes. Rinse with water to remove.

Stop use and ask a doctorif rash occurs

Keep out of reach of children.If product is swallowed, get medical help or contact a Poison Control Center right away.

Directions

For sunscreen use:

- apply liberally 15 minutes before sun exposure
- use a water resistant sunscreen if swimming or sweating
- reapply at least every 2 hours
- Sun Protection Measures. Spending time in the sun increases your risk of skin cancer and early skin aging. To decrease this risk, regularly use a sunscreen with a broad spectrum SPF of 15 or higher and other sun protection measures including:
  - limit time in the sun, especially from 10 a.m. – 2 p.m.
  - wear long-sleeve shirts, pants, hats, and sunglasses
- children under 6 months: Ask a doctor

Inactive Ingredients

WATER, BUTYLENE GLYCOL, GLYCERIN, DIPROPYLENE GLYCOL, DIMETHICONE, GLYCERYL STEARATE SE, BEHENYL ALCOHOL, PEG/PPG-14/7 DIMETHYL ETHER, POLYBUTYLENE GLYCOL/PPG-9/1 COPOLYMER, HYDROGENATED POLYDECENE, ISOPROPYL MYRISTATE, MYRISTYL MYRISTATE, MICROCRYSTALLINE WAX, PEG-40 STEARATE, SILICA, CARNOSINE, XANTHAN GUM, ERYTHRITOL, TOCOPHERYL ACETATE, POTASSIUM ASCORBYL TOCOPHERYL PHOSPHATE, PANTHENYL ETHYL ETHER, SODIUM ACETYLATED HYALURONATE, SORBITAN TRISTEARATE, STEARYL ALCOHOL, CELLULOSE GUM, SODIUM METAPHOSPHATE, TRISODIUM EDTA, BHT, SODIUM METABISULFITE, TOCOPHEROL, PHENOXYETHANOL, FRAGRANCE, IRON OXIDES,

Other information

- protect this product in this container from excessive heat and direct sun.

Questions or comments?

Call toll free 1-800-906-7503

SHISEIDO AMERICA INC.
NEW YORK, N.Y. 10022
SHISEIDO DIST.
NEW YORK • PARIS • MILANO

PRINCIPAL DISPLAY PANEL - 50 mL Jar Carton

SHI SEIDO

BENEFIANCE
NutriPerfect

Day Cream

BROAD SPECTRUM
SPF 18

SUNSCREEN

PRO-FORTIFYING
Carnosine DP™

50mL NET WT. 1.8 OZ.